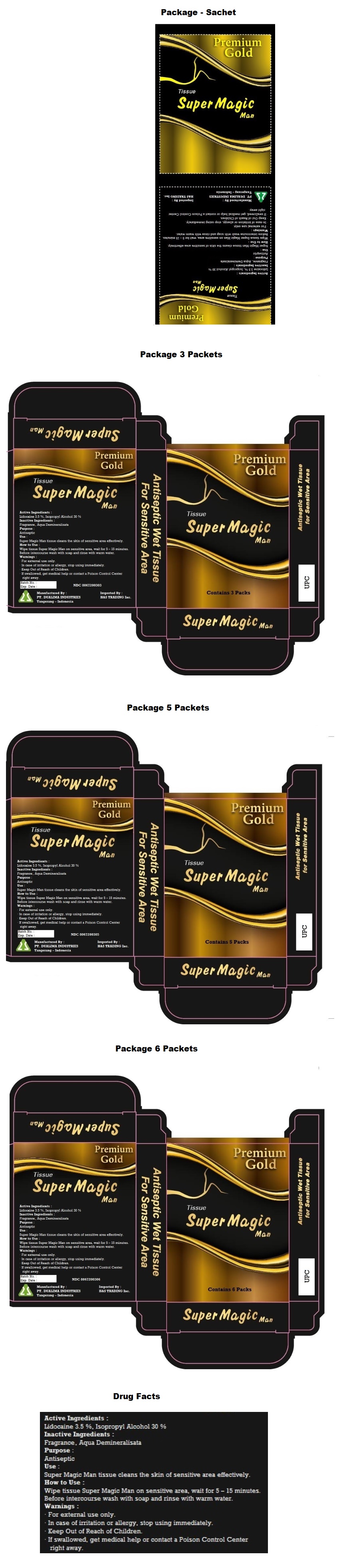 DRUG LABEL: Super Magic Man Premium Gold
NDC: 80672-003 | Form: CLOTH
Manufacturer: PT. DUALIMA INDUSTRIES
Category: otc | Type: HUMAN OTC DRUG LABEL
Date: 20201008

ACTIVE INGREDIENTS: LIDOCAINE 3.5 g/100 mL; ISOPROPYL ALCOHOL 30 mL/100 mL
INACTIVE INGREDIENTS: WATER

Super Magic Man PREMIUM GOLD Tissue

Active Ingredients :

Lidocaine 3.5%

Isopropyl Alcohol 30%

Purpose :

Antiseptic

Use :

Super Magic Man tissue cleans the skin of sensitive area effectively.

Warnings :

• For external use only.

• In case of irritation or allergy, stop using immediately.

Keep Out of Reach of Children. If swallowed, get medical help or contact a Poison Control Center right away.

How to Use:

Wipe tissue Super Magic Man tissue on sensitive area, wait for 5 - 15 minutes. Before intercourse wash with soap and rinse with warm water.

Inactive ingredients

Fragrance, Aqua Demineralisata

Antiseptic Wet Tissue

For Sensitive Area

Imported By:

H&S Trading Inc.

Manufactured By:

PT. DUALIMA INDUSTRIES

Tangerang - Indonesia